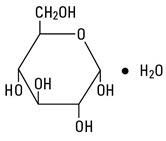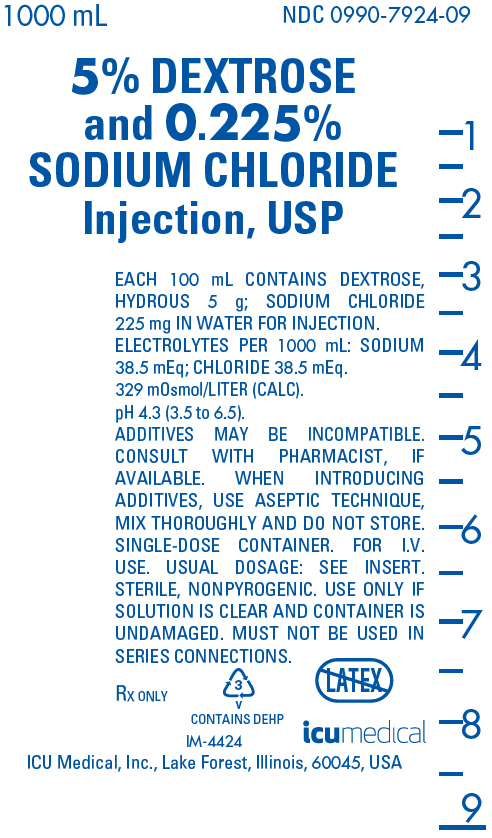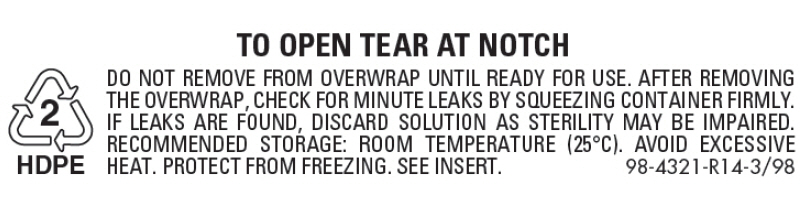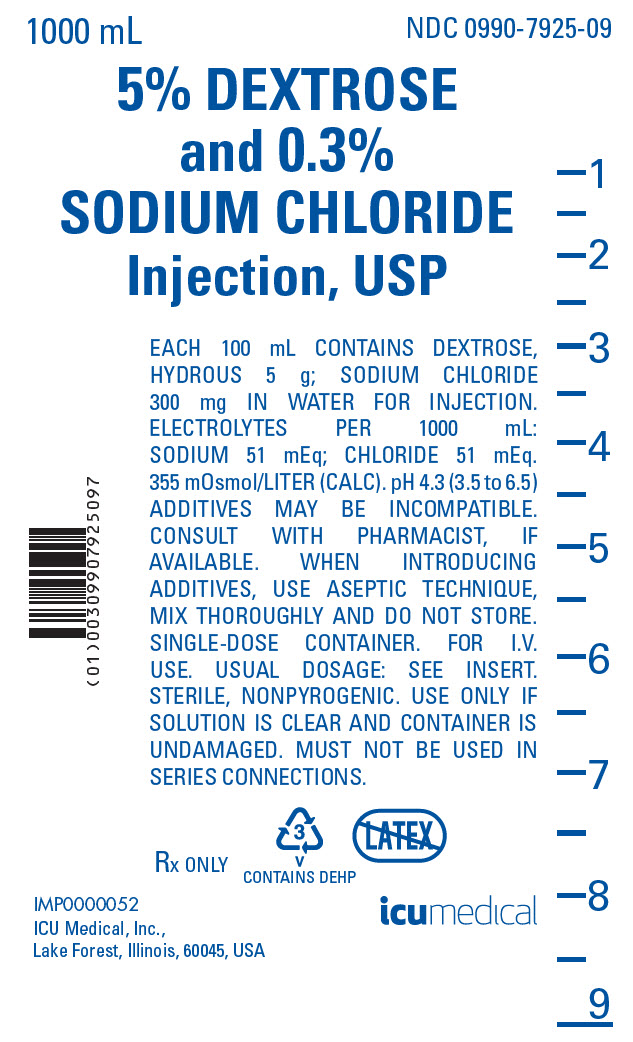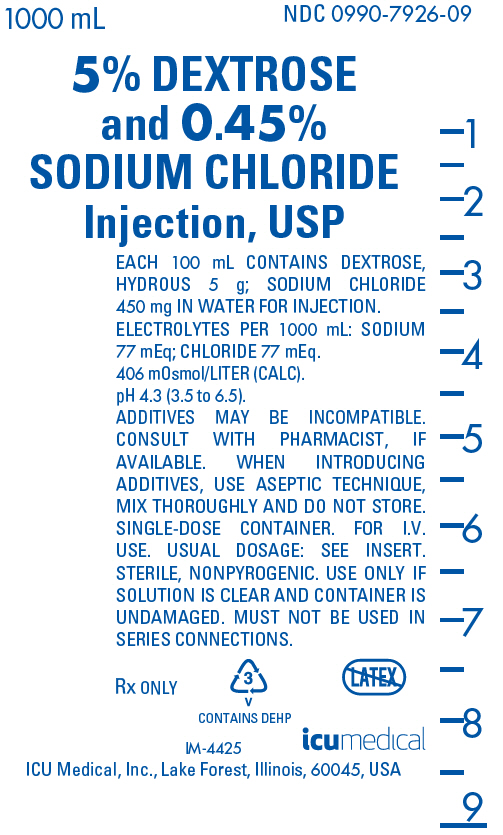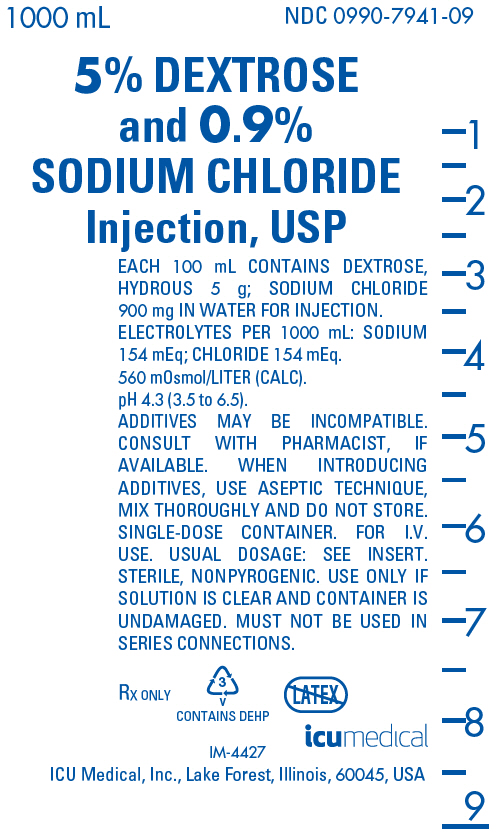 DRUG LABEL: Dextrose and Sodium Chloride
NDC: 0990-7924 | Form: INJECTION, SOLUTION
Manufacturer: ICU Medical Inc.
Category: prescription | Type: HUMAN PRESCRIPTION DRUG LABEL
Date: 20251102

ACTIVE INGREDIENTS: DEXTROSE MONOHYDRATE 5 g/100 mL; SODIUM CHLORIDE 0.225 g/100 mL
INACTIVE INGREDIENTS: WATER

Dextrose and Sodium Chloride
Injection, USP

Flexible Plastic Container

Rx only

DESCRIPTION

Dextrose and Sodium Chloride Injection, USP solutions are sterile and nonpyrogenic. They are large volume parenteral solutions containing various concentrations and combinations of these drugs in water for injection intended for intravenous administration.

See Table for summary of content and characteristics of these solutions.

The solutions contain no bacteriostat, antimicrobial agent or added buffer and each is intended only as a single-dose injection. When smaller doses are required the unused portion should be discarded.

The solutions are parenteral fluid, nutrient and electrolyte replenishers.

Dextrose, USP is chemically designated D-glucose monohydrate (C6H12O6 • H2O), a hexose sugar freely soluble in water. It has the following structural formula:

Sodium Chloride, USP is chemically designated NaCl, a white crystalline powder freely soluble in water.

Water for Injection, USP is chemically designated H2O.

The flexible plastic container is fabricated from a specially formulated polyvinylchloride. Water can permeate from inside the container into the overwrap but not in amounts sufficient to affect the solution significantly. Solutions in contact with the plastic container may leach out certain chemical components from the plastic in very small amounts; however, biological testing was supportive of the safety of the plastic container materials. Exposure to temperatures above 25°C/77°F during transport and storage will lead to minor losses in moisture content. Higher temperatures lead to greater losses. It is unlikely that these minor losses will lead to clinically significant changes within the expiration period.

CLINICAL PHARMACOLOGY

When administered intravenously, these solutions provide a source of water, carbohydrate and electrolytes.

Solutions which provide combinations of hypotonic or isotonic concentrations of dextrose and of sodium chloride are suitable for parenteral maintenance or replacement of water and electrolyte requirements with minimal carbohydrate calories.

Solutions containing carbohydrate in the form of dextrose restore blood glucose levels and provide calories. Carbohydrate in the form of dextrose may aid in minimizing liver glycogen depletion and exerts a protein-sparing action. Dextrose injected parenterally undergoes oxidation to carbon dioxide and water.

Sodium chloride in water dissociates to provide sodium (Na^+) and chloride (Cl¯) ions. Sodium (Na^+) is the principal cation of the extracellular fluid and plays a large part in the therapy of fluid and electrolyte disturbances. Chloride (Cl¯) has an integral role in buffering action when oxygen and carbon dioxide exchange occurs in the red blood cells. The distribution and excretion of sodium (Na^+) and chloride (Cl¯) are largely under the control of the kidney which maintains a balance between intake and output.

Water is an essential constituent of all body tissues and accounts for approximately 70% of total body weight. Average normal adult daily requirements range from two to three liters (1.0 to 1.5 liters each for insensible water loss by perspiration and urine production). Water balance is maintained by various regulatory mechanisms. Water distribution depends primarily on the concentration of electrolytes in the body compartments and sodium (Na^+) plays a major role in maintaining physiologic equilibrium.

INDICATIONS AND USAGE

Intravenous solutions containing dextrose and sodium chloride are indicated for parenteral replenishment of fluid, minimal carbohydrate calories, and sodium chloride as required by the clinical condition of the patient.

CONTRAINDICATIONS

None known.

WARNINGS

Solutions containing sodium ions should be used with great care, if at all, in patients with congestive heart failure, severe renal insufficiency and in clinical states in which there exists edema with sodium retention.

Excessive administration of potassium-free solutions may result in significant hypokalemia.

In patients with diminished renal function, administration of solutions containing sodium ions may result in sodium retention.

The intravenous administration of these solutions can cause fluid and/or solute overloading resulting in dilution of serum electrolyte concentrations, overhydration, congested states or pulmonary edema.

The risk of dilutional states is inversely proportional to the electrolyte concentrations of administered parenteral solutions. The risk of solute overload causing congested states with peripheral and pulmonary edema is directly proportional to the electrolyte concentrations of such solutions.

PRECAUTIONS

Clinical evaluation and periodic laboratory determinations are necessary to monitor changes in fluid balance, electrolyte concentrations and acid-base balance during prolonged parenteral therapy or whenever the condition of the patient warrants such evaluation.

Solutions containing dextrose should be used with caution in patients with known subclinical or overt diabetes mellitus.

Caution must be exercised in the administration of parenteral fluids, especially those containing sodium ions to patients receiving corticosteroids or corticotropin.

Do not administer unless solution is clear and container is undamaged. Discard unused portion.

Pregnancy Category C. Animal reproduction studies have not been conducted with dextrose or sodium chloride. It is also not known whether dextrose or sodium chloride can cause fetal harm when administered to a pregnant woman or can affect reproduction capacity. Dextrose or sodium chloride should be given to a pregnant woman only if clearly needed.

Pediatric Use. The safety and effectiveness in the pediatric population are based on the similarity of the clinical conditions of the pediatric and adult populations. In neonates or very small infants, the volume of fluid may affect fluid and electrolyte balance.

Frequent monitoring of serum glucose concentrations is required when dextrose is prescribed to pediatric patients, particularly neonates and low birth weight infants.

In very low birth weight infants, excessive or rapid administration of dextrose injection may result in increased serum osmolality and possible intracerebral hemorrhage.

Geriatric Use. An evaluation of current literature revealed no clinical experience identifying differences in response between elderly and younger patients. In general, dose selection for an elderly patient should be cautious, usually starting at the low end of the dosing range, reflecting the greater frequency of decreased hepatic, renal, or cardiac function, and of concomitant disease or other drug therapy. Sodium ions are known to be substantially excreted by the kidney, and the risk of toxic reactions may be greater in patients with impaired renal function. Because elderly patients are more likely to have decreased renal function, care should be taken in dose selection, and it may be useful to monitor renal function.

ADVERSE REACTIONS

Reactions which may occur because of the solution or the technique of administration include febrile response, infection at the site of injection, venous thrombosis or phlebitis extending from the site of injection, extravasation and hypervolemia.

If an adverse reaction does occur, discontinue the infusion, evaluate the patient, institute appropriate therapeutic countermeasures and save the remainder of the fluid for examination if deemed necessary.

OVERDOSAGE

In the event of overhydration or solute overload, re-evaluate the patient and institute appropriate corrective measures. See WARNINGS, PRECAUTIONS, and ADVERSE REACTIONS.

DOSAGE AND ADMINISTRATION

The dose is dependent upon the age, weight and clinical condition of the patient.

As reported in the literature, the dosage and constant infusion rate of intravenous dextrose must be selected with caution in pediatric patients, particularly neonates and low birth weight infants, because of the increased risk of hyperglycemia/hypoglycemia.

Parenteral drug products should be inspected visually for particulate matter and discoloration prior to administration, whenever solution and container permit. See PRECAUTIONS.

Drug Interactions

Additives may be incompatible. Consult with pharmacist, if available. When introducing additives, use aseptic technique, mix thoroughly and do not store.

INSTRUCTIONS FOR USE

To Open:

Tear outer wrap at notch and remove solution container. If supplemental medication is desired, follow directions below before preparing for administration.

To Add Medication

1. Prepare additive port.
2. Using aseptic technique and an additive delivery needle of appropriate length, puncture resealable additive port at target area, inner diaphragm and inject. Withdraw needle after injecting medication.
3. The additive port may be protected by covering with an additive cap.
4. Mix container contents thoroughly.

Preparation for Administration
(Use aseptic technique)

1. Close flow control clamp of administration set.
2. Remove cover from outlet port at bottom of container.
3. Insert piercing pin of administration set into port with a twisting motion until the set is firmly seated. NOTE: When using a vented administration set, replace bacterial retentive air filter with piercing pin cover. Insert piercing pin with twisting motion until shoulder of air filter housing rests against the outlet port flange.
4. Suspend container from hanger.
5. Squeeze and release drip chamber to establish proper fluid level in chamber.
6. Attach venipuncture device to set.
7. Open clamp to expel air from set and venipuncture device. Close clamp.
8. Perform venipuncture.
9. Regulate rate of administration with flow control clamp.

WARNING: Do not use flexible container in series connections.

HOW SUPPLIED

Dextrose and Sodium Chloride Injection, USP are supplied in single-dose flexible plastic containers in various sizes and concentrations as shown in the accompanying Table.

Content and Characteristics
 |  | Grams/100 mL |  | Per 1000 mL
NDC No. | Product | Dextrose; (hydrous) | Sodium; Chloride | Sodium; Na^+ | Chloride; Cl¯ | Caloric; Value | Tonicity | Osmolarity mOsmol/L (calc) | pH | Container; size (mL)
0409-7924-02 [Manufactured by ICU Medical, Inc., Lake Forest, Illinois, 60045, USA] 0990-7924-02 | 5% Dextrose and 0.225% Sodium Chloride Inj., USP | 5 | 0.225 | 38.5 mEq | 38.5 mEq | 170 | Hypertonic | 329 | 4.3 (3.5 to 6.5) | 250
0409-7924-03 [Manufactured for ICU Medical, Inc., Lake Forest, Illinois, 60045, USA] 0990-7924-03, | 5% Dextrose and 0.225% Sodium Chloride Inj., USP | 5 | 0.225 | 38.5 mEq | 38.5 mEq | 170 | Hypertonic | 329 | 4.3 (3.5 to 6.5) | 500
0409-7924-09, 0990-7924-09, | 5% Dextrose and 0.225% Sodium Chloride Inj., USP | 5 | 0.225 | 38.5 mEq | 38.5 mEq | 170 | Hypertonic | 329 | 4.3 (3.5 to 6.5) | 1000
0409-7925-03 0990-7925-03, | 5% Dextrose and 0.3% Sodium Chloride Inj., USP | 5 | 0.3 | 51 mEq | 51 mEq | 170 | Hypertonic | 355 | 4.3 (3.5 to 6.5) | 500
0409-7925-09, 0990-7925-09, | 5% Dextrose and 0.3% Sodium Chloride Inj., USP | 5 | 0.3 | 51 mEq | 51 mEq | 170 | Hypertonic | 355 | 4.3 (3.5 to 6.5) | 1000
0409-7926-02 0990-7926-02 | 5% Dextrose and 0.45% Sodium Chloride Inj., USP | 5 | 0.45 | 77 mEq | 77 mEq | 170 | Hypertonic | 406 | 4.3 (3.5 to 6.5) | 250
0409-7926-03 0990-7926-03, | 5% Dextrose and 0.45% Sodium Chloride Inj., USP | 5 | 0.45 | 77 mEq | 77 mEq | 170 | Hypertonic | 406 | 4.3 (3.5 to 6.5) | 500
0409-7926-09, 0990-7926-09, | 5% Dextrose and 0.45% Sodium Chloride Inj., USP | 5 | 0.45 | 77 mEq | 77 mEq | 170 | Hypertonic | 406 | 4.3 (3.5 to 6.5) | 1000
0409-7941-03 0990-7941-03, | 5% Dextrose and 0.9% Sodium Chloride Inj., USP | 5 | 0.9 | 154 mEq | 154 mEq | 170 | Hypertonic | 560 | 4.3 (3.5 to 6.5) | 500
0409-7941-09, 0990-7941-09, | 5% Dextrose and 0.9% Sodium Chloride Inj., USP | 5 | 0.9 | 154 mEq | 154 mEq | 170 | Hypertonic | 560 | 4.3 (3.5 to 6.5) | 1000

ICU Medical is transitioning NDC codes from "0409" to "0990" labeler code. Both NDC codes are expected to be in the market for a period of time.

Protect from freezing. Store at 20 to 25°C (68 to 77°F). [See USP Controlled Room Temperature.]

Revised: August, 2020

IFU0000261

PRINCIPAL DISPLAY PANEL - 1000 mL Bag Label - NDC 0990-7924-09

1000 mL
NDC 0990-7924-09

5% DEXTROSE
and 0.225%
SODIUM CHLORIDE
Injection, USP

EACH 100 mL CONTAINS DEXTROSE,
HYDROUS 5 g; SODIUM CHLORIDE
225 mg IN WATER FOR INJECTION.
ELECTROLYTES PER 1000 mL: SODIUM
38.5 mEq; CHLORIDE 38.5 mEq.
329 mOsmol/LITER (CALC).
pH 4.3 (3.5 to 6.5).
ADDITIVES MAY BE INCOMPATIBLE.
CONSULT WITH PHARMACIST, IF
AVAILABLE. WHEN INTRODUCING
ADDITIVES, USE ASEPTIC TECHNIQUE,
MIX THOROUGHLY AND DO NOT STORE.
SINGLE-DOSE CONTAINER. FOR I.V.
USE. USUAL DOSAGE: SEE INSERT.
STERILE, NONPYROGENIC. USE ONLY IF
SOLUTION IS CLEAR AND CONTAINER IS
UNDAMAGED. MUST NOT BE USED IN
SERIES CONNECTIONS.

Rx ONLY

3
V
CONTAINS DEHP

IM-4424

icumedical

ICU Medical, Inc., Lake Forest, Illinois, 60045, USA

PRINCIPAL DISPLAY PANEL - 1000 mL Bag Overwrap - NDC 0990-7924-09

2
HDPE

TO OPEN TEAR AT NOTCH

DO NOT REMOVE FROM OVERWRAP UNTIL READY FOR USE. AFTER REMOVING
THE OVERWRAP, CHECK FOR MINUTE LEAKS BY SQUEEZING CONTAINER FIRMLY.
IF LEAKS ARE FOUND, DISCARD SOLUTION AS STERILITY MAY BE IMPAIRED.
RECOMMENDED STORAGE: ROOM TEMPERATURE (25°C). AVOID EXCESSIVE
HEAT. PROTECT FROM FREEZING. SEE INSERT.
98-4321-R14-3/98

PRINCIPAL DISPLAY PANEL - 1000 mL Bag Label - NDC 0990-7925-09

1000 mL
NDC 0990-7925-09

5% DEXTROSE
and 0.3%
SODIUM CHLORIDE
Injection, USP

EACH 100 mL CONTAINS DEXTROSE,
HYDROUS 5 g; SODIUM CHLORIDE
300 mg IN WATER FOR INJECTION.
ELECTROLYTES PER 1000 mL:
SODIUM 51 mEq; CHLORIDE 51 mEq.
355 mOsmol/LITER (CALC). pH 4.3 (3.5 to 6.5)
ADDITIVES MAY BE INCOMPATIBLE.
CONSULT WITH PHARMACIST, IF
AVAILABLE. WHEN INTRODUCING
ADDITIVES, USE ASEPTIC TECHNIQUE,
MIX THOROUGHLY AND DO NOT STORE.
SINGLE-DOSE CONTAINER. FOR I.V.
USE. USUAL DOSAGE: SEE INSERT.
STERILE, NONPYROGENIC. USE ONLY IF
SOLUTION IS CLEAR AND CONTAINER IS
UNDAMAGED. MUST NOT BE USED IN
SERIES CONNECTIONS.

Rx ONLY

3
V
CONTAINS DEHP

IMP0000052

icumedical

ICU Medical, Inc.,
Lake Forest, Illinois, 60045, USA

PRINCIPAL DISPLAY PANEL - 1000 mL Bag Label - NDC 0990-7926-09

1000 mL
NDC 0990-7926-09

5% DEXTROSE
and 0.45%
SODIUM CHLORIDE
Injection, USP

EACH 100 mL CONTAINS DEXTROSE,
HYDROUS 5 g; SODIUM CHLORIDE
450 mg IN WATER FOR INJECTION.
ELECTROLYTES PER 1000 mL: SODIUM
77 mEq; CHLORIDE 77 mEq.
406 mOsmol/LITER (CALC).
pH 4.3 (3.5 to 6.5).
ADDITIVES MAY BE INCOMPATIBLE.
CONSULT WITH PHARMACIST, IF
AVAILABLE. WHEN INTRODUCING
ADDITIVES, USE ASEPTIC TECHNIQUE,
MIX THOROUGHLY AND DO NOT STORE.
SINGLE-DOSE CONTAINER. FOR I.V.
USE. USUAL DOSAGE: SEE INSERT.
STERILE, NONPYROGENIC. USE ONLY IF
SOLUTION IS CLEAR AND CONTAINER IS
UNDAMAGED. MUST NOT BE USED IN
SERIES CONNECTIONS.

Rx ONLY

3
V
CONTAINS DEHP

icumedical

IM-4425

ICU Medical, Inc., Lake Forest, Illinois, 60045, USA

PRINCIPAL DISPLAY PANEL - 1000 mL Bag Label - NDC 0990-7941-09

1000 mL
NDC 0990-7941-09

5% DEXTROSE
and 0.9%
SODIUM CHLORIDE
Injection, USP

EACH 100 mL CONTAINS DEXTROSE,
HYDROUS 5 g; SODIUM CHLORIDE
900 mg IN WATER FOR INJECTION.
ELECTROLYTES PER 1000 mL: SODIUM
154 mEq; CHLORIDE 154 mEq.
560 mOsmol/LITER (CALC).
pH 4.3 (3.5 to 6.5)
ADDITIVES MAY BE INCOMPATIBLE.
CONSULT WITH PHARMACIST, IF
AVAILABLE. WHEN INTRODUCING
ADDITIVES, USE ASEPTIC TECHNIQUE,
MIX THOROUGHLY AND DO NOT STORE.
SINGLE-DOSE CONTAINER. FOR I.V.
USE. USUAL DOSAGE: SEE INSERT.
STERILE, NONPYROGENIC. USE ONLY IF
SOLUTION IS CLEAR AND CONTAINER IS
UNDAMAGED. MUST NOT BE USED IN
SERIES CONNECTIONS.

Rx ONLY

3
V
CONTAINS DEHP

icumedical

IM-4427

ICU Medical, Inc., Lake Forest, Illinois, 60045, USA